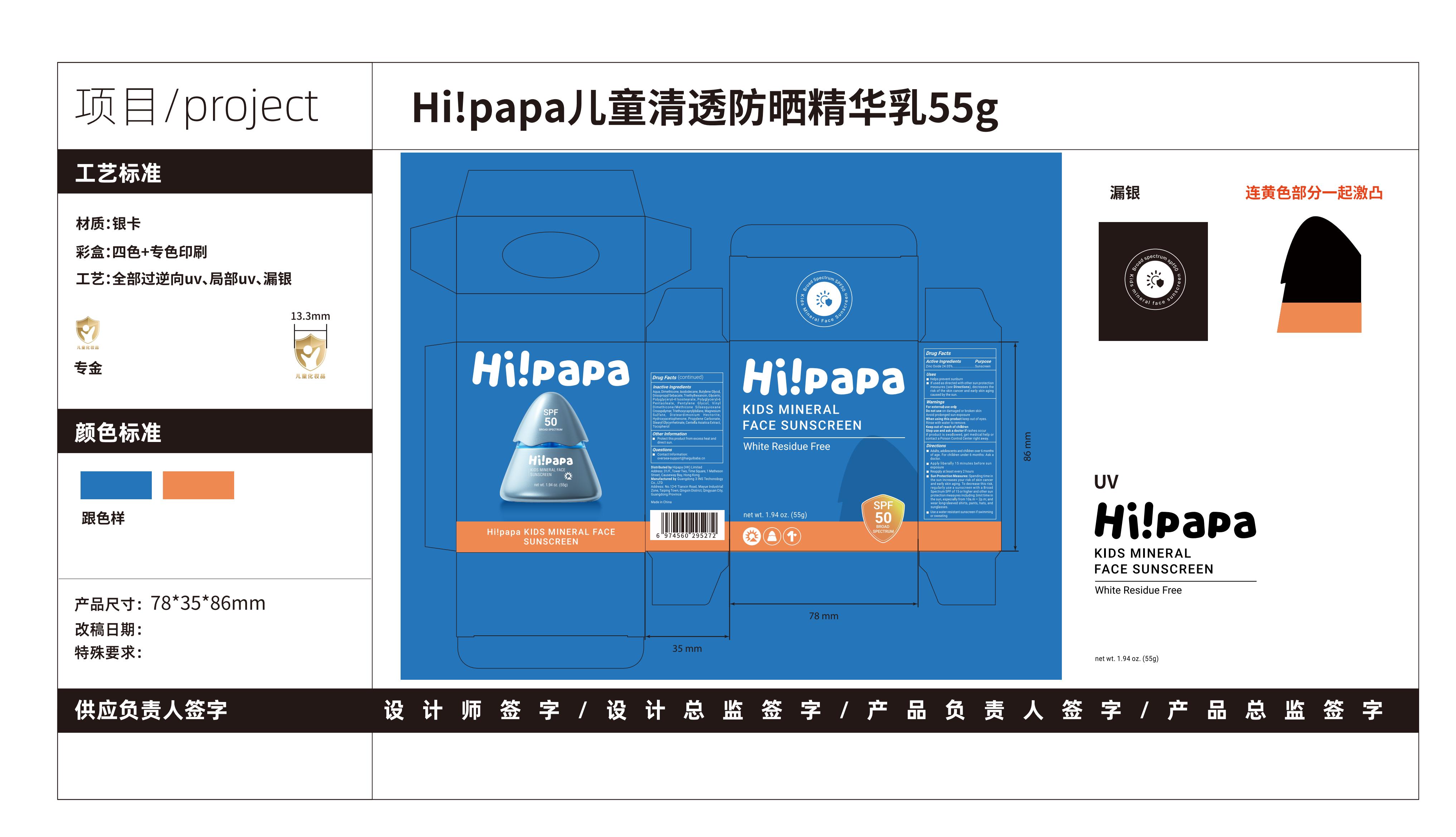 DRUG LABEL: Hi papa KIDS MINERAL FACE SUNSCREEN
NDC: 75779-008 | Form: CREAM
Manufacturer: GUANG DONG 3 INS TECHNOLOGY Co., Ltd
Category: otc | Type: HUMAN OTC DRUG LABEL
Date: 20250212

ACTIVE INGREDIENTS: ZINC OXIDE 24.05 g/100 g
INACTIVE INGREDIENTS: BUTYLENE GLYCOL; PROPYLENE CARBONATE; STEARYL GLYCYRRHETINATE; VINYL DIMETHICONE/METHICONE SILSESQUIOXANE CROSSPOLYMER; DIMETHICONE; HYDROXYACETOPHENONE; CENTELLA ASIATICA ROOT; POLYGLYCERYL-4 ISOSTEARATE; ISODODECANE; POLYGLYCERYL-6 POLYRICINOLEATE; PENTYLENE GLYCOL; TOCOPHEROL; MAGNESIUM SULFATE; DISTEARDIMONIUM HECTORITE; TRIETHOXYCAPRYLYLSILANE; GLYCERIN; TRIETHYLHEXANOIN; AQUA; DIISOPROPYL SEBACATE

75779-008

Active Ingredient

Zinc Oxide 24.05%

Purpose

Sunscreen

Use

Helps prevent sunburn
If used as directed with other sun protection measures(see Directions),decreases the risk of the skin cancer and early skin aging caused by the sun.

Warnings

For external use only

Do not use on damaged or broken skin
Avoid prolonged sun exposure

When Using

When using this product keep out of eyes.
Rinse with water to remove.

Stop Use

Stop use and ask a doctor if rashes occur

Ask Doctor

Stop use and ask a doctor if rashes occur
For children under 6 months: Ask adoctor.

Keep Oot Of Reach Of Children

Keep out of reach of children
If product is swallowed, get medical help or contact a Poison Control Center right away.

Directions

Adults, adolescents and children over 6 months of age. For children under 6 months: Ask a doctor.
Apply liberally 15 minutes before sun exposure
Reapply at least every 2 hours
Sun Protection Measures: Spending time in the sun increases your risk of skin cancer and early skin aging. To decrease this risk,regularly use a sunscreen with a Broad Spectrum SPF of 15 or higher and other sun protection measures including:limit time in the sun,especially from 10a.m-2p.m; and wear long-sleeved shirts, pants, hats, and sunglasses.
Use a water resistant sunscreen if swimming or sweating

Other information

Protect this product from excess heat and direct sun.

Inactive ingredients

Aqua,Dimethicone,Isododecane,Butylene Glycol,Diisopropyl Sebacate,Triethylhexanoin,Glycerin,Polyglyceryl-4 Isostearate,Polyglyceryl-6 Pentaoleate,Pentylene Glycol,Vinyl Dimethicone/Methicone Silsesquioxane Crosspolymer,Triethoxycaprylylsilane,Magnesium Sulfate,Disteardimonium Hectorite,Hydroxyacetophenone,Propylene Carbonate,Stearyl Glycyrrhetinate,Centella Asiatica Extract,Tocopherol

Questions

Contact Information:
oversea-support@haiguibaba.cn